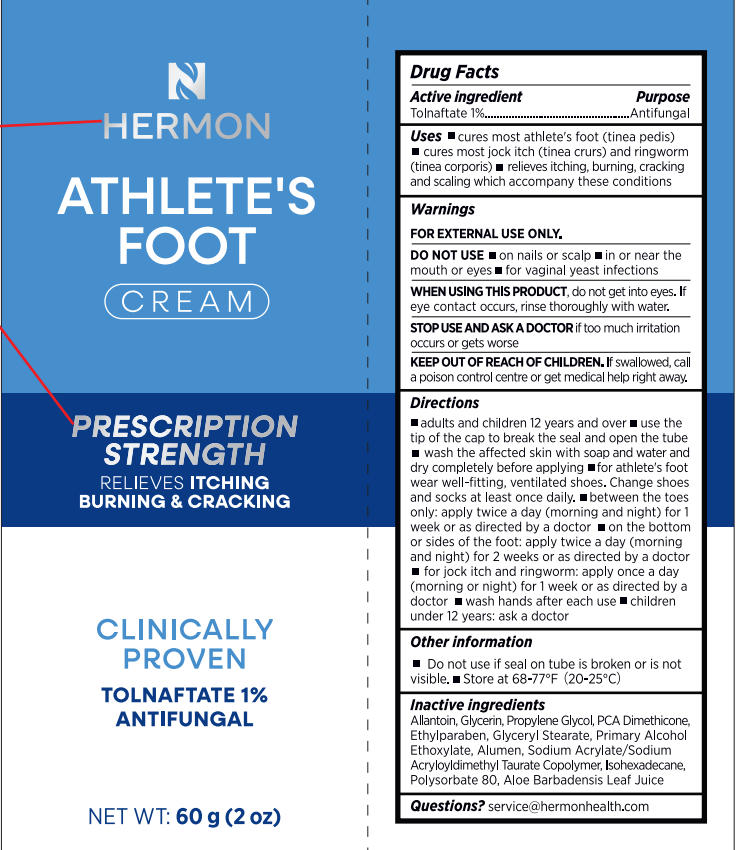 DRUG LABEL: Initial Drug Listing - Hermon Athletes foot 1% tolnaftate cream
NDC: 85398-017 | Form: CREAM
Manufacturer: Beautivity LLC
Category: otc | Type: HUMAN OTC DRUG LABEL
Date: 20251021

ACTIVE INGREDIENTS: TOLNAFTATE 0.6 g/60 g
INACTIVE INGREDIENTS: ALOE BARBADENSIS LEAF JUICE; PROPYLENE GLYCOL; GLYCERYL STEARATE; SODIUM ACRYLATE/SODIUM ACRYLOYLDIMETHYLTAURATE COPOLYMER (4000000 MW); ALCOHOL; POTASSIUM ALUM; GLYCERIN; HYDROXYETHYL ACRYLATE/SODIUM ACRYLOYLDIMETHYL TAURATE COPOLYMER (45000 MPA.S AT 1%); POLYSORBATE 80; ALLANTOIN; ISOHEXADECANE; DIMETHICONE 6; ETHYLPARABEN

Initial Drug Listing - Hermon Athlete‘s foot 1% tolnaftate cream

ACTIVE INGREDIENT

Tolnaftate 1%

PURPOSE

Antifungal

DOSAGE AND ADMINISTRATION

- cures most athlete's foot (tinea pedis)
- cures most jock itch (tinea crurs) and ringworm(tinea corporis)
- relieves itching, burning, cracking and scaling which accompany these conditions

WARNINGS

FOR EXTERNAL USE ONLY

DO NOT USE

- on nails or scalp
- in or near themouth or eyes
- for vaginal yeast infections

WHEN USING

do not get into eyes. lf eye contact occurs, rinse thoroughly with water

ASK DOCTOR

if too much irritationo ccurs or gets worse

KEEP OUT OF REACH OF CHILDREN

lf swallowed, call a poison control centre or get medical help right away.

INDICATIONS AND USAGE

- adults and children 12 years and over
- use the tip of the cap to break the seal and open the tube
- wash the affected skin with soap and water and dry completely before applying
- for athlete's foot wear well-fitting, ventilated shoes. Change shoes and socks at least once daily
- between the toesonly: apply twice a day(morning and night) for 1week or as directed by a doctor
- on the bottomor sides of the foot: apply twice a day(morningand night)for 2 weeks or as directed by a doctor
- for jock itch and ringworm: apply once a day(morning or night) for 1 week or as directed by adoctor
- wash hands after each use
- children under 12 years: ask a doctor

- Do not use if seal on tube is broken or is not visible.
- Store at 68-77°F(20-25°C)

INACTIVE INGREDIENT

Allantoin, Glycerin, Propylene Glycol, PCA Dimethicone, Ethylparaben, Glyceryl Stearate, Primary Alcohol, Ethoxylate,Alumen, Sodium Acrylate/Sodium, Acryloyldimethyl Taurate Copolymer, lsohexadecane,Polysorbate 80, Aloe Barbadensis Leaf Juice

QUESTIONS

service@hermonhealth.com